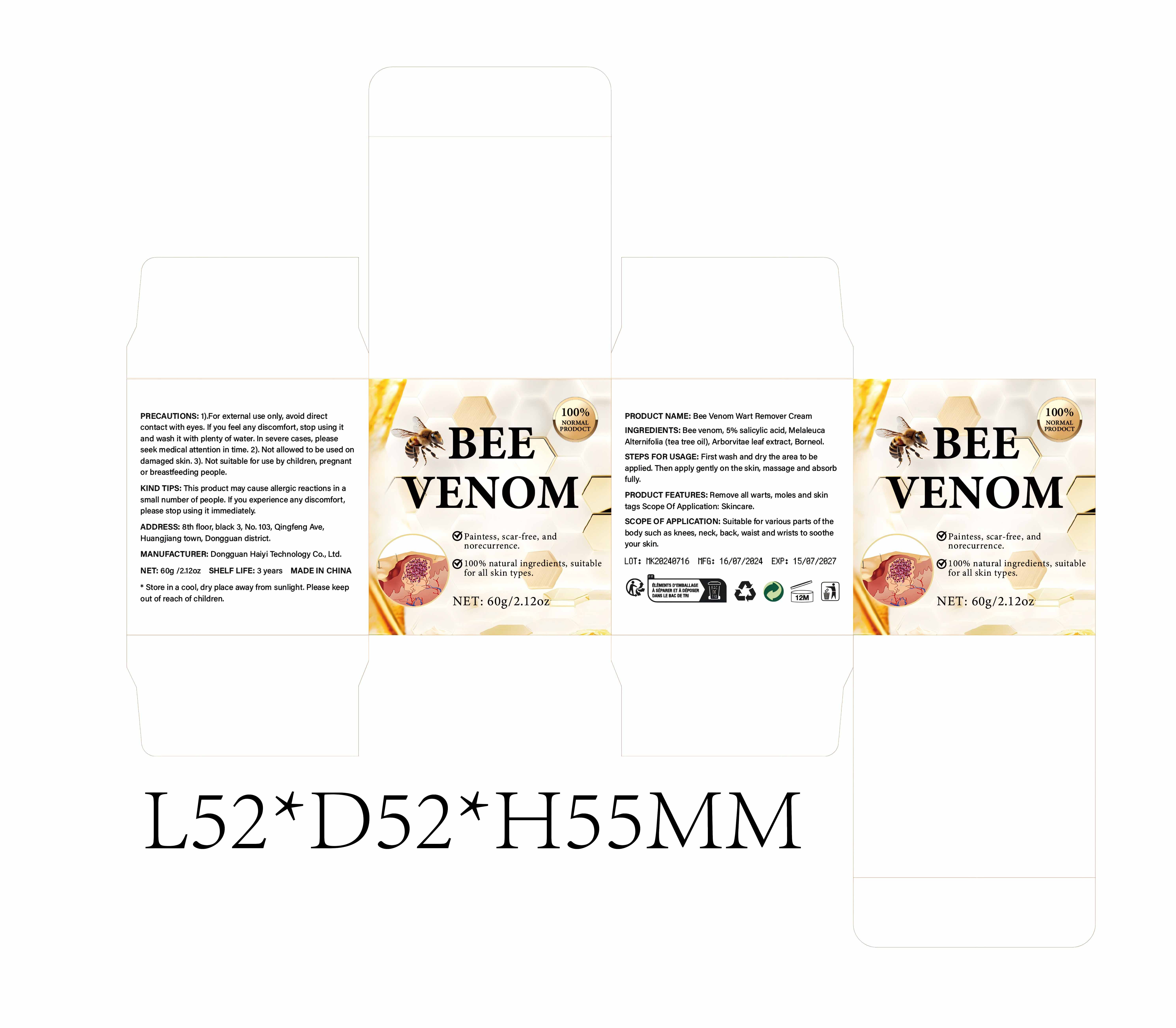 DRUG LABEL: Bee Venom Wart Remover Cream
NDC: 84732-003 | Form: CREAM
Manufacturer: Dongguan Haiyi Technology Co.,Ltd.
Category: otc | Type: HUMAN OTC DRUG LABEL
Date: 20240920

ACTIVE INGREDIENTS: 5-METHOXYSALICYLIC ACID 5 g/100 g
INACTIVE INGREDIENTS: THUJA OCCIDENTALIS LEAF; BEE POLLEN; MELALEUCA ALTERNIFOLIA LEAF; BORNEOL

Active ingredient

salicylic acid

Inactive ingredient

Bee venom

Melaleuca Alternifolia(tea tree oil)

Arborvitae leaf extract

Borneol

Purpose section

Remove all warts, moles and skintags

Warning

1).For external use only, avoid directcontact with eyes, lf you feel any discomfort, stop using itand wash it with plenty of water. In severe cases, pleaseseekmedical attention in time.

2). Not allowed to be used ondamaged skin

stop use

This product may cause allergic reactions in asmall number of people. lf you experience any discomfort,please stop using it immediately.

not use

Not suitable for use by children, pregnantor breastfeeding people.

OUT OF CHILDREN

KEEP THE PRODUCT OUT OF REACH OF CHILDREN to

HOW TO USE

First wash and dry the area to beapplied. Then apply gently on the skin, massage and absorbfully.

Dosage

take an appropriateamount,Use 2-3 times a week